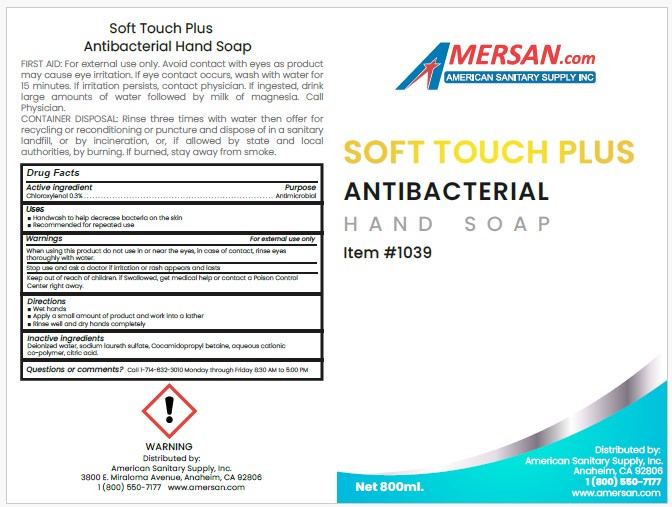 DRUG LABEL: SOFT TOUCH PLUS ANTIBACTERIAL HAND

NDC: 50536-139 | Form: SOAP
Manufacturer: AMERICAN CHEMICAL AND SANITARY SUPPLY INC
Category: otc | Type: HUMAN OTC DRUG LABEL
Date: 20250423

ACTIVE INGREDIENTS: CHLOROXYLENOL 0.3 g/100 mL
INACTIVE INGREDIENTS: ANHYDROUS CITRIC ACID; ACRYLATES CROSSPOLYMER-4; COCAMIDOPROPYL BETAINE; SODIUM LAURETH SULFATE; WATER

ACSS (as PLD) - SOFT TOUCH PLUS ANTIBACTERIAL HAND SOAP, ITEM #1039 (50536-139)

ACTIVE INGREDIENT

Chloroxylenol 0.3%

PURPOSE

ANTIMICROBIAL

USES

- Handwash to help decrease bacteria on the skin
- Recommended for repeated use

WARNINGS

FOR EXTERNAL USE ONLY.

When using this product do not use in or near the eyes, in case of contact, rinse eyes thoroughly with water.

Stop use and ask a doctor if irritation or rash appears and lasts

Keep out of reach of children. if Swallowed, get medical help or contact a Poison Control Center right away.

DIRECTIONS

- Wet hands
- Apply a small amount of product and work into a lather
- Rinse well and dry hands completely

INACTIVE INGREDIENTS

Deionized water, sodium laureth sulfate, Cocamidopropyl betaine, aqueous cationic co-polymer, citric acid.

Questions or comments?

Call 1-714-632-3010 Monday through Friday 8:30 AM to 5:00 PM